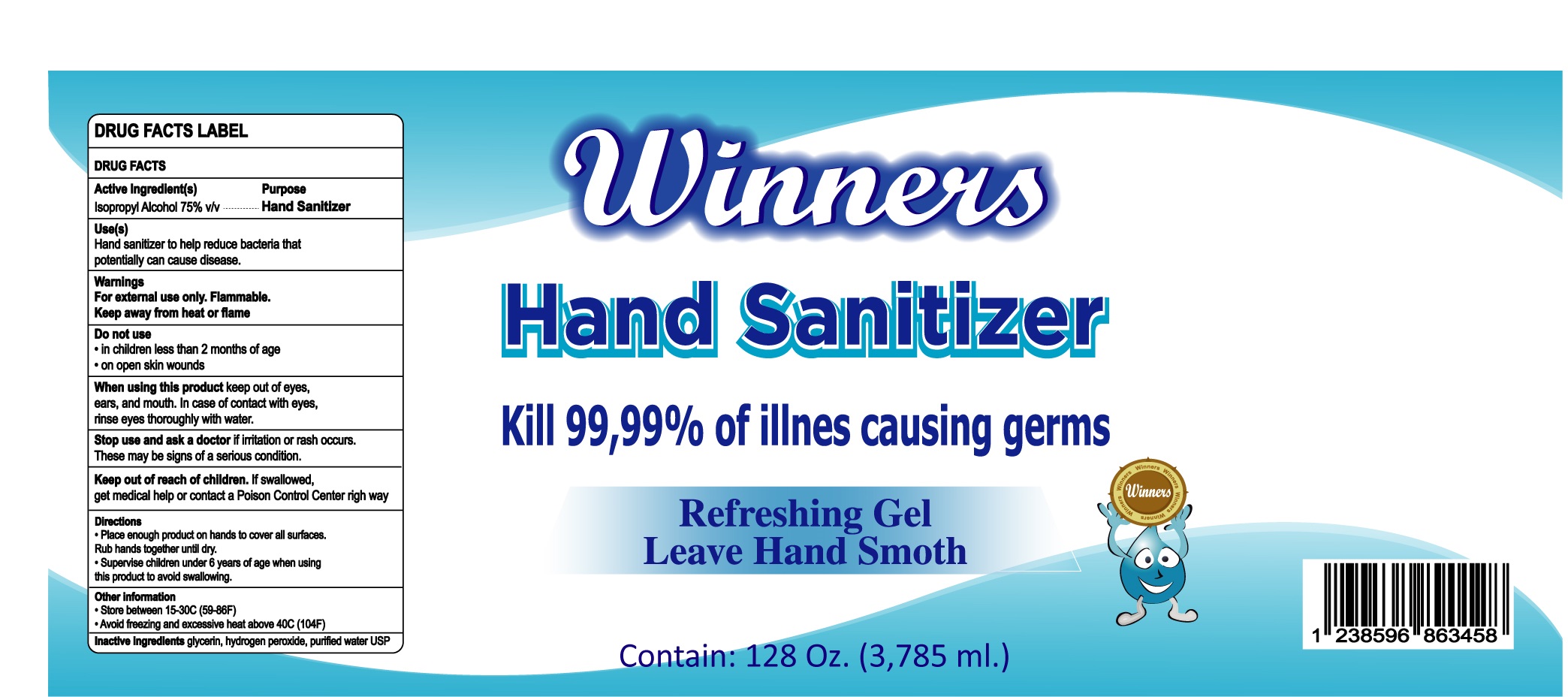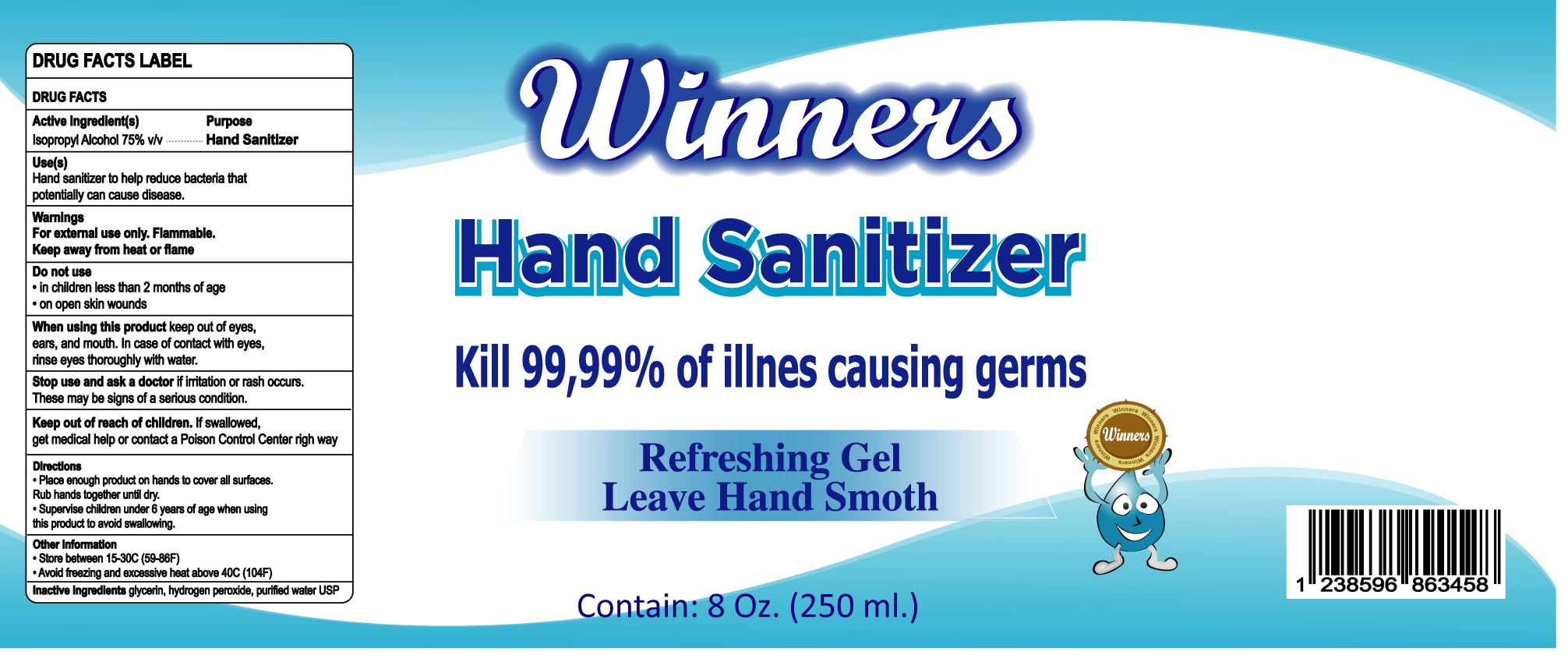 DRUG LABEL: Winners hand Sanitizer
NDC: 79343-001 | Form: GEL
Manufacturer: Ecoquimica RLP, S.R.L.
Category: otc | Type: HUMAN OTC DRUG LABEL
Date: 20200812

ACTIVE INGREDIENTS: ISOPROPYL ALCOHOL 0.75 mL/1 mL
INACTIVE INGREDIENTS: GLYCERIN; HYDROGEN PEROXIDE; WATER

Winners hand Sanitizer

Active Ingredient[s]

Isopropyl Alcohol 75% v/v

Purpose

Hand Sanitizer

Uses[s]

Hand sanitizer to help reduce bacteria that potentially can cause disease.

Warnings

For external use only. Flammable.

Keep away from heat or flame.

Do not use

- in children less than 2 months of age
- on open skin wounds

When using this product

keep out of eyes, ears, and mouth. In case of contact with eyes, rinse eyes thoroughly with water

Stop use and ask a doctor

if irritation or rash occurs. These may be signs of a serious condition.

Keep out of reach of children.

If swallowed, get medical help or contact a Poison Control Center right away

Directions

- Place enough product on hands to cover all surfaces. Rub hands together until dry.
- Supervise children under 6 years of age when using this product to avoid swallowing.

Other information

- Store between 15-30C (59-86F)
- Avoid freezing and excessive heat above 40C (104F)

Inactive ingredients

glycerin, hydrogen peroxide, purified water USP